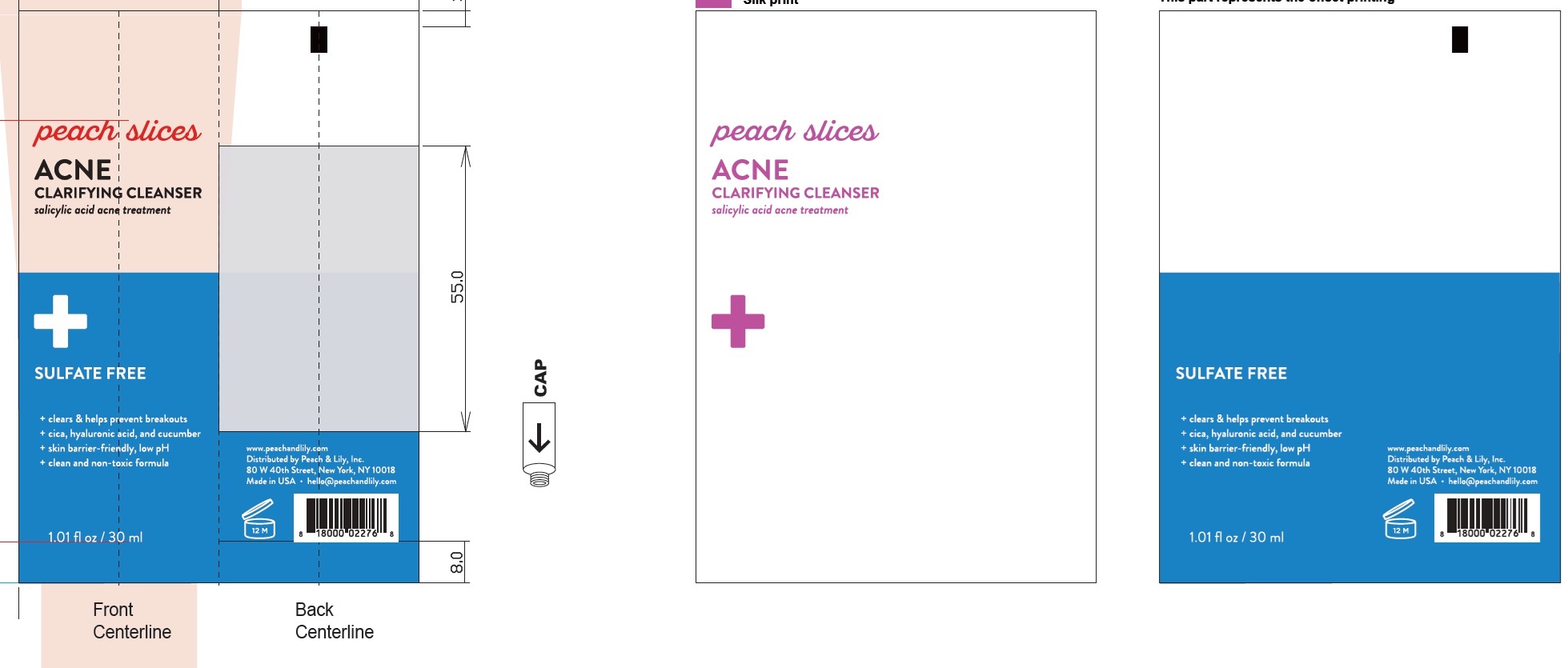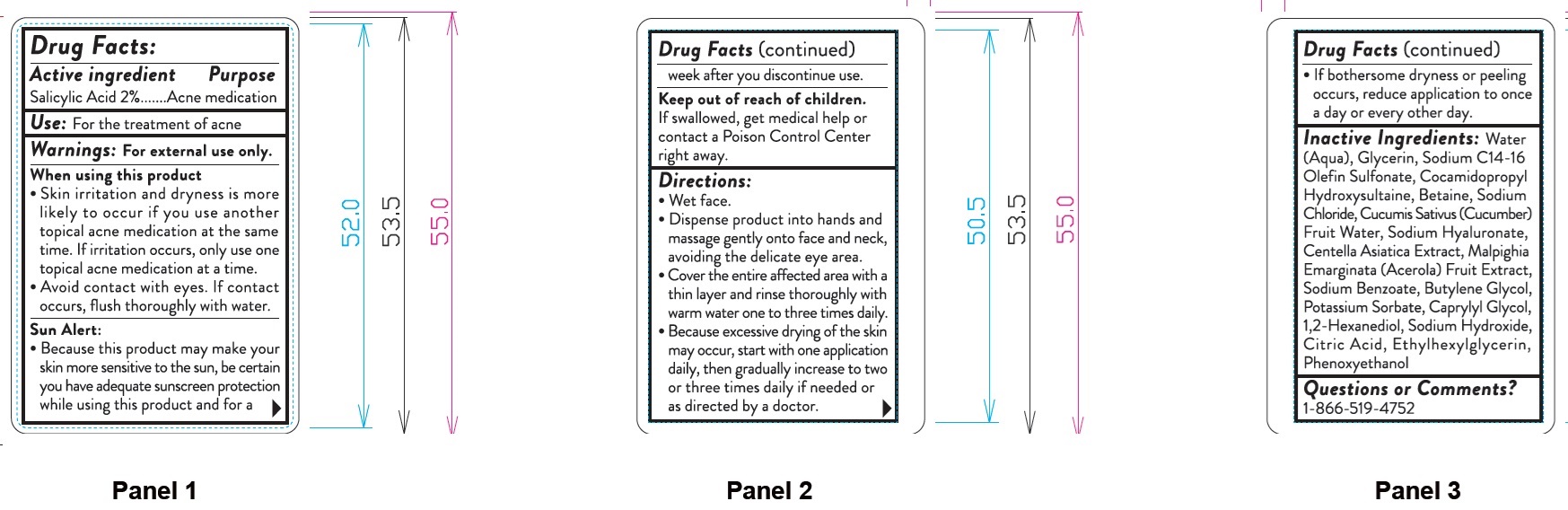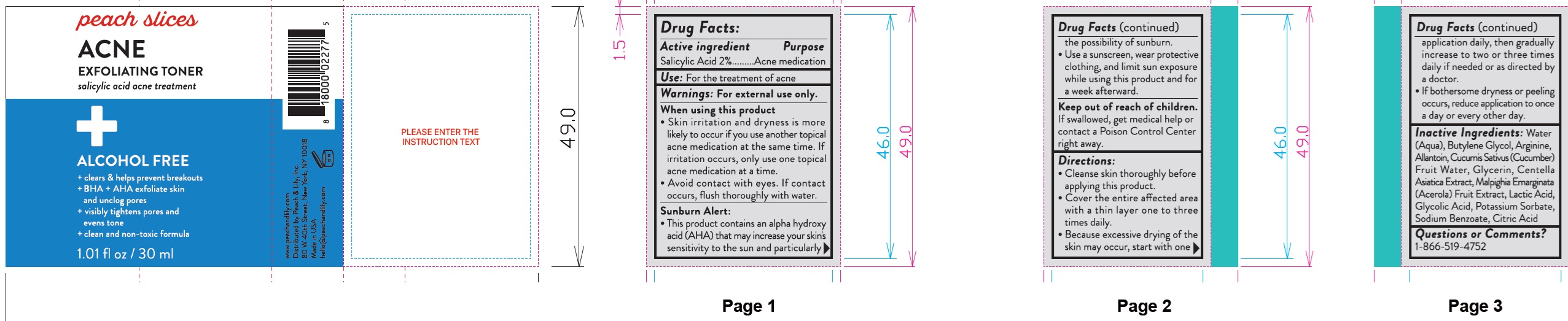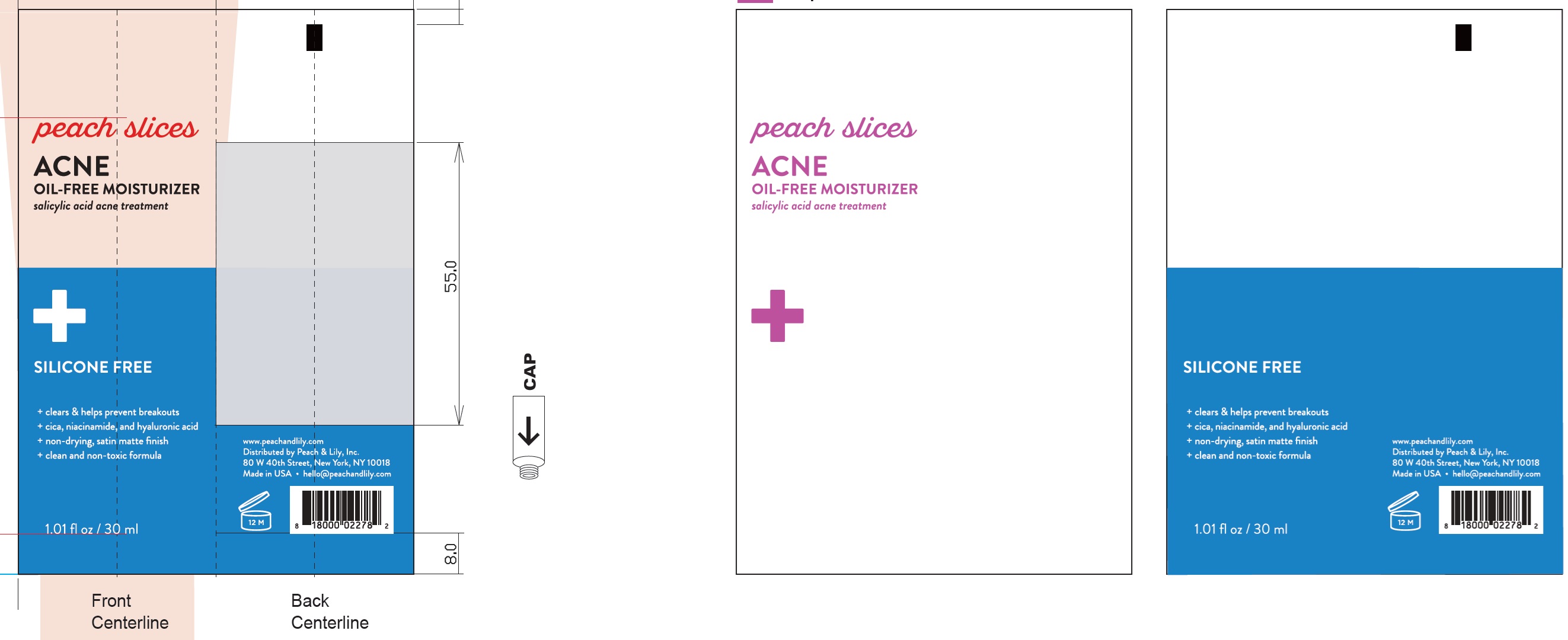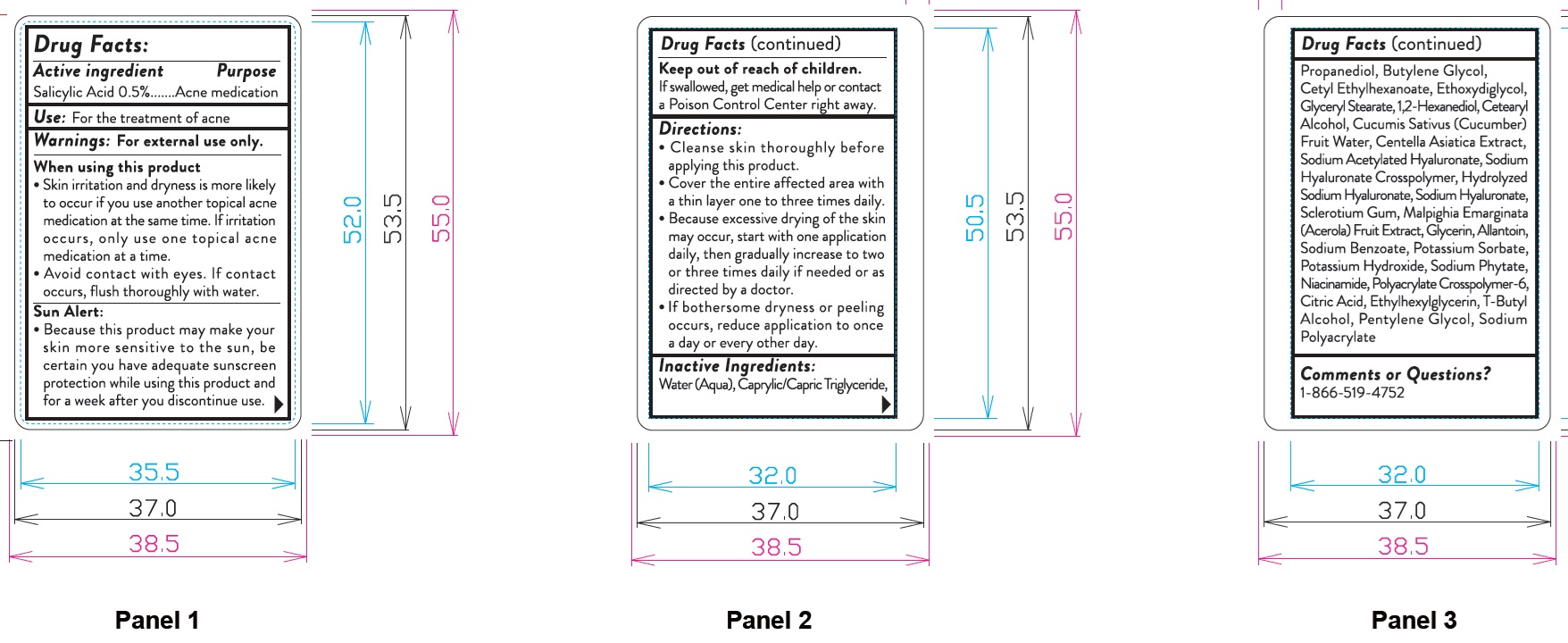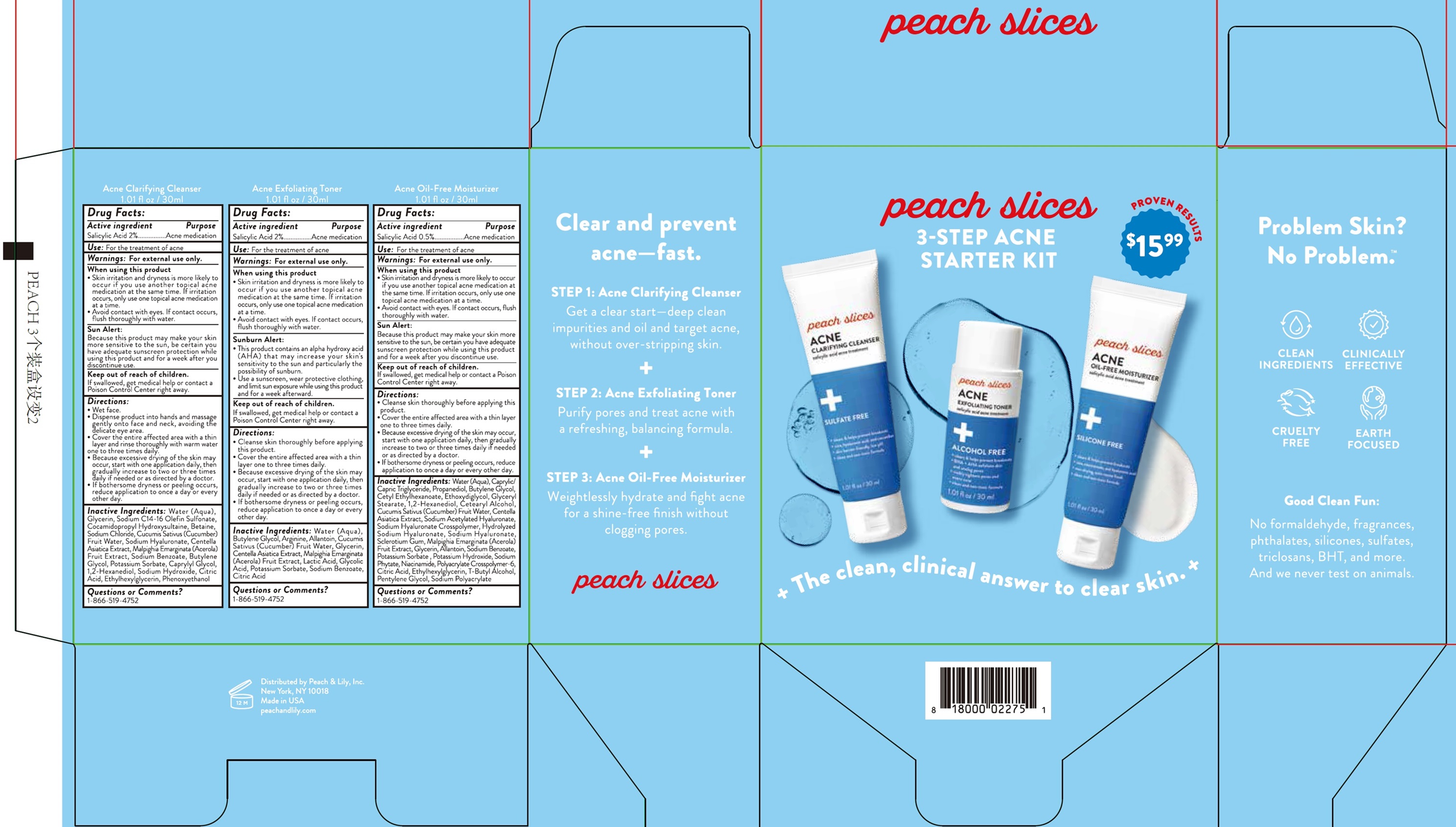 DRUG LABEL: Peach Slices 3 Step Acne Starter Kit
NDC: 81515-540 | Form: KIT | Route: TOPICAL
Manufacturer: Peach & Lily, Inc
Category: otc | Type: HUMAN OTC DRUG LABEL
Date: 20240814

ACTIVE INGREDIENTS: SALICYLIC ACID 20 mg/1 mL; SALICYLIC ACID 20 mg/1 mL; SALICYLIC ACID 5 mg/1 mL
INACTIVE INGREDIENTS: WATER; GLYCERIN; SODIUM C14-16 OLEFIN SULFONATE; COCAMIDOPROPYL HYDROXYSULTAINE; BETAINE; SODIUM CHLORIDE; CUCUMBER FRUIT OIL; HYALURONATE SODIUM; CENTELLA ASIATICA TRITERPENOIDS; ACEROLA; SODIUM BENZOATE; BUTYLENE GLYCOL; POTASSIUM SORBATE; CAPRYLYL GLYCOL; 1,2-HEXANEDIOL; SODIUM HYDROXIDE; CITRIC ACID MONOHYDRATE; ETHYLHEXYLGLYCERIN; PHENOXYETHANOL; WATER; BUTYLENE GLYCOL; ARGININE; ALLANTOIN; CUCUMBER FRUIT OIL; GLYCERIN; CENTELLA ASIATICA TRITERPENOIDS; ACEROLA; LACTIC ACID, UNSPECIFIED FORM; GLYCOLIC ACID; POTASSIUM SORBATE; SODIUM BENZOATE; CITRIC ACID MONOHYDRATE; WATER; MEDIUM-CHAIN TRIGLYCERIDES; PROPANEDIOL; BUTYLENE GLYCOL; CETYL ETHYLHEXANOATE; DIETHYLENE GLYCOL MONOETHYL ETHER; GLYCERYL MONOSTEARATE; 1,2-HEXANEDIOL; CETOSTEARYL ALCOHOL; CUCUMBER FRUIT OIL; CENTELLA ASIATICA TRITERPENOIDS; SODIUM ACETYLATED HYALURONATE; HYALURONATE SODIUM; BETASIZOFIRAN; ACEROLA; GLYCERIN; ALLANTOIN; SODIUM BENZOATE; POTASSIUM SORBATE; POTASSIUM HYDROXIDE; PHYTATE SODIUM; NIACINAMIDE; AMMONIUM ACRYLOYLDIMETHYLTAURATE, DIMETHYLACRYLAMIDE, LAURYL METHACRYLATE AND LAURETH-4 METHACRYLATE COPOLYMER, TRIMETHYLOLPROPANE TRIACRYLATE CROSSLINKED (45000 MPA.S); CITRIC ACID MONOHYDRATE; ETHYLHEXYLGLYCERIN; TERT-BUTYL ALCOHOL; PENTYLENE GLYCOL

Peach Slices. 3 Step Acne Starter Kit

Active ingredient

Salicylic Acid 2%

Purpose

Acne medication

Use:

For the treatment of acne

Warnings:

For external use only.

When using this product

- Skin irritation and dryness is more likely to occur if you use another topical acne medication at the same time. If irritation occurs, only use one topical acne medication at a time.
- Avoid contact with eyes. If contact occurs, flush thoroughly with water.

Sun Alert:

Because this product may make your skin more sensitive to the sun, be certain you have adequate sunscreen protection while using this product and for a week after you discontinue use.

Keep out of reach of children.

If swallowed, get medical help or contact a Poison Control Center right away.

Directions:

- Wet face.
- Dispense product into hands and massage gently onto face and neck, avoiding the delicate eye area.
- Cover the entire affected area with a thin layer and rinse thoroughly with warm water one to three times daily.
- Because excessive drying of the skin may occur, start with one application daily, then gradually increase to two or three times daily if needed or as directed by a doctor.
- If bothersome dryness or peeling occurs, reduce application to once a day or every other day.

Inactive Ingredients:

Water (Aqua), Glycerin, Sodium C14-16 Olefin Sulfonate, Cocamidopropyl Hydroxysultaine, Betaine, Sodium Chloride, Cucumis Sativus (Cucumber) Fruit Water, Sodium Hyaluronate, Centella Asiatica Extract, Malpighia Emarginata (Acerola) Fruit Extract, Sodium Benzoate, Butylene Glycol, Potassium Sorbate, Caprylyl Glycol, 1,2-Hexanediol, Sodium Hydroxide, Citric Acid, Ethylhexylglycerin, Phenoxyethanol

Questions or Comments?

1-866-519-4752

Active ingredient

Salicylic Acid 2%

Purpose

Acne medication

Use:

For the treatment of acne

Warnings:

For external use only.

When using this product

- Skin irritation and dryness is more likely to occur if you use another topical acne medication at the same time. If irritation occurs, only use one topical acne medication at the same time. If irritation occurs, only use one topical medication at a time.
- Avoid contact with eyes. If contact occurs, flush thoroughly with water.

Sunburn Alert:

- This product contains an alpha hydroxy acid (AHA) that may increase your skin's sensitivity to the sun and particularly the possibility of sunburn.
- Use a sunscreen, wear protective clothing, and limit sun exposure while using this product and for a week afterward.

Keep out of reach of children.

If swallowed, get medical help or contact a Poison Control Center right away.

Directions:

- Cleanse skin thoroughly before applying this product.
- Cover the entire affected area with a thin layer one to three times daily.
- Because excessive drying of the skin may occur, start with one application daily, then gradually increase to two or three times daily if needed or as directed by a doctor.
- If bothersome dryness or peeling occurs, reduce application to once a day or every other day.

Inactive Ingredients:

Water (Aqua), Butylene Glycol, Arginine, Allantoin, Cucumis Sativus (Cucumber) Fruit Water, Glycerin, Centella Asiatica Extract, Malpighia Emarginata (Acerola) Fruit Extract, Lactic Acid, Glycolic Acid, Potassium Sorbate, Sodium Benzoate, Citric Acid

Questions or Comments?

1-866-519-4752

Active ingredient

Salicylic Acid 0.5%

Purpose

Acne medication

Use:

For the treatment of acne

Warnings:

For external use only.

When using this product

- Skin irritation and dryness is more likely to occur if you use another topical acne medication at the same time. If irritation occurs, only use one topical acne medication at the same time. If irritation occurs, only use one topical medication at a time.
- Avoid contact with eyes. If contact occurs, flush thoroughly with water

Sun Alert:

Because this product may make your skin more sensitive to the sun, be certain you have adequate sunscreen protection while using this product and for a week after you discontinue use.

Keep out of reach of children.

If swallowed, get medical help or contact a Poison Control Center right away.

Directions:

- Cleanse skin thoroughly before applying this product.
- Cover the entire affected area with a thin layer one to three times daily.
- Because excessive drying of the skin may occur, start with one application daily, then gradually increase to two or three times daily if needed or as directed by a doctor.
- If bothersome dryness or peeling occurs, reduce application to once a day or every other day.

Inactive Ingredients:

Water (Aqua), Caprylic/Capric Triglyceride, Propanediol, Butylene Glycol, Cetyl Ethylhexanoate, Ethoxydiglycol, Glyceryl Stearate, 1,2-Hexanediol, Cetearyl Alcohol, Cucumis Sativus (Cucumber) Fruit Water, Centella Asiatica Extract, Sodium Acetylated Hyaluronate, Sodium Hydrolyzed Crosspolymer, Hydrolyzed Sodium Hyaluronate, Sodium Hyaluronate, Sclerotium Gum, Malpighia Emarginata (Acerola) Fruit Extract, Glycerin, Allantoin, Sodium Benzoate, Potassium Sorbate, Potassium Hydroxide, Sodium Phytate, Niacinamide, Polyacrylate Crosspolymer-6, Citric Acid, Ethylhexylglycerin, T-Butyl Alcohol, Pentylene GLycol, Sodium Polyacrylate

Questions or Comments?

1-866-519-4752